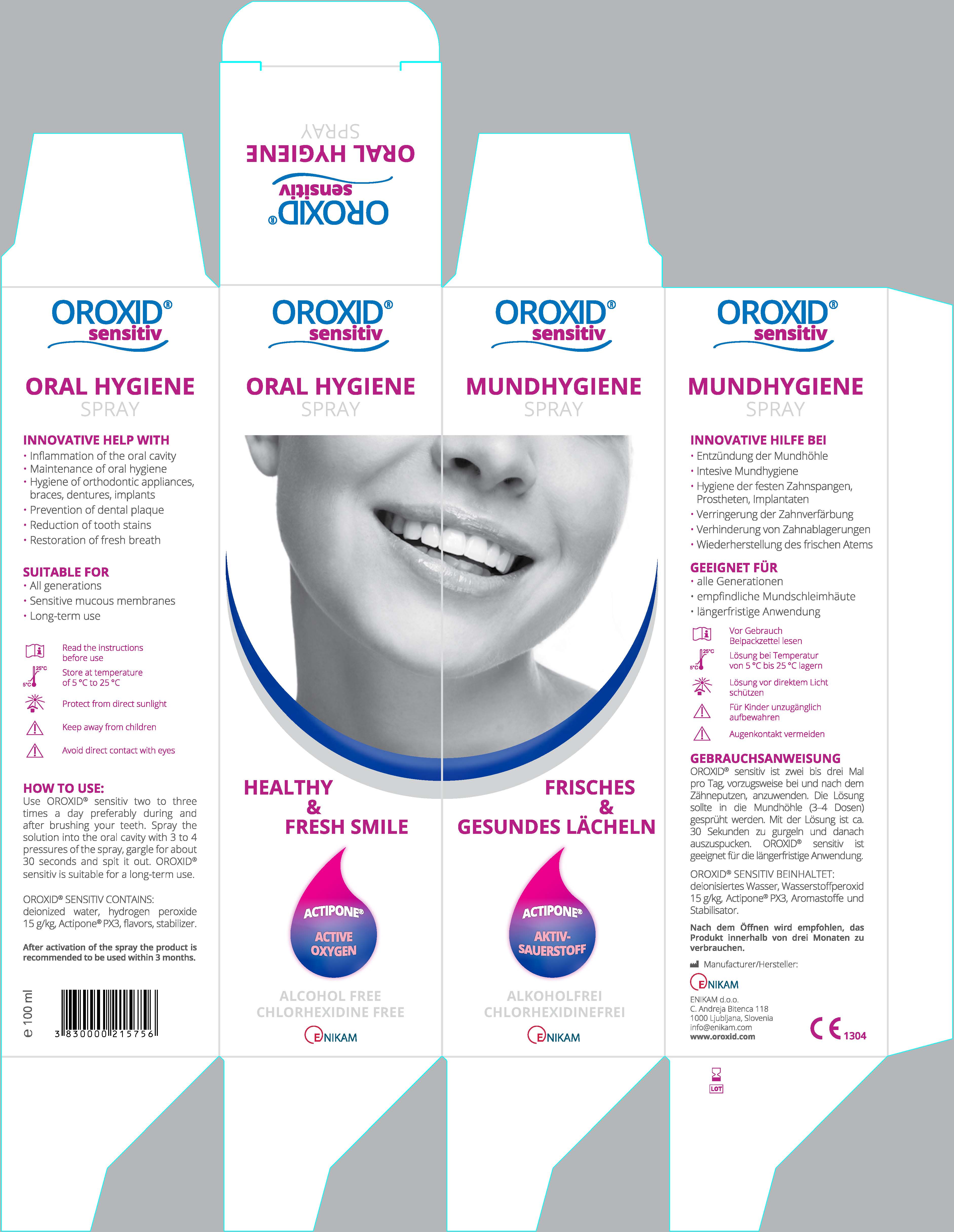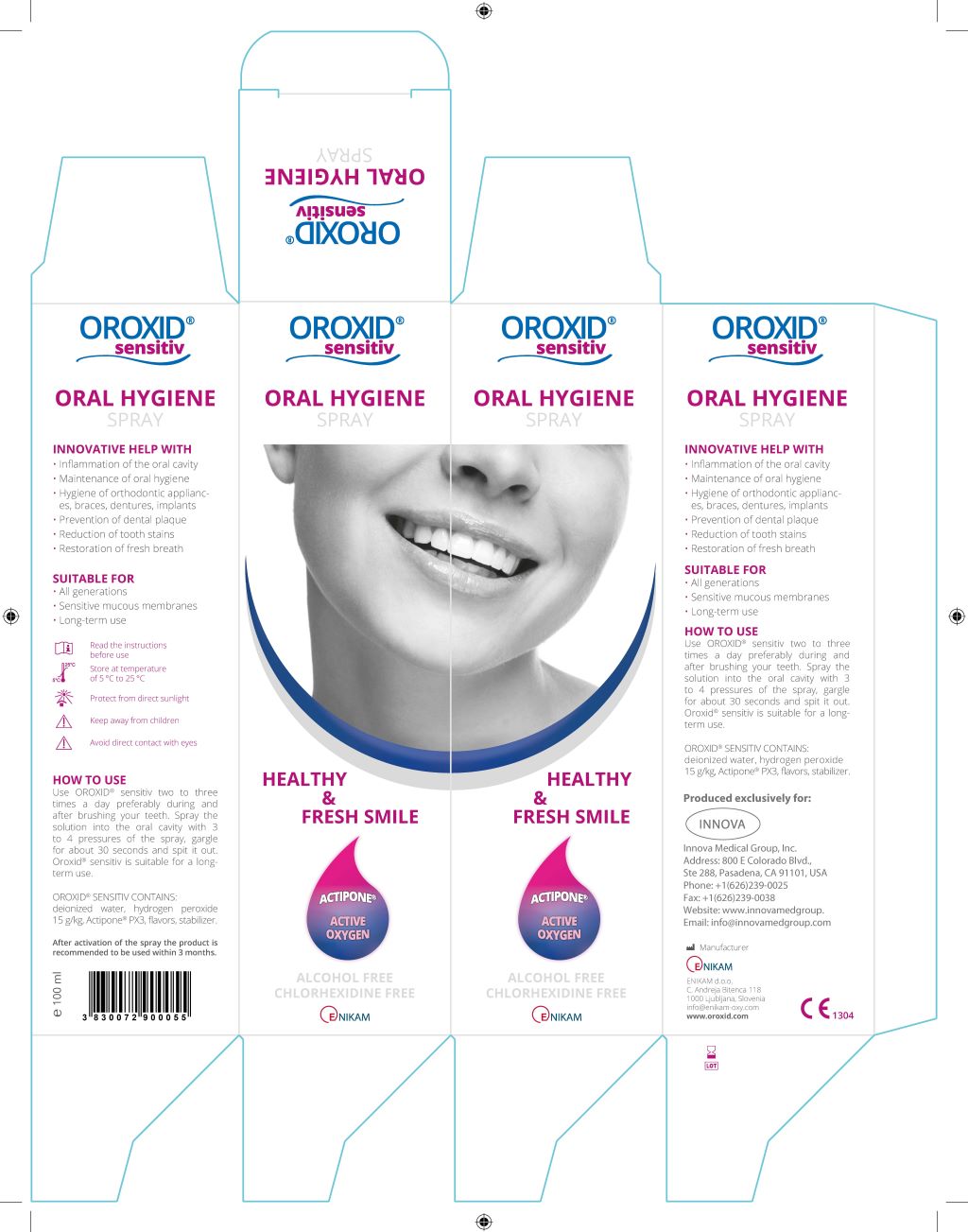 DRUG LABEL: OROXID Sensitiv
NDC: 81794-600 | Form: SOLUTION
Manufacturer: Innova Medical Group
Category: otc | Type: HUMAN OTC DRUG LABEL
Date: 20210724

ACTIVE INGREDIENTS: HYDROGEN PEROXIDE 1.5 mL/1.5 mL
INACTIVE INGREDIENTS: GINGER; ECHINACEA PURPUREA WHOLE; COMMIPHORA MYRRHA STEM BARK; PEG-40 CASTOR OIL; SPEARMINT; WATER; STEVIA EUPATORIA WHOLE

Instruction For use

Use OROXID® sensitiv two to three times a day preferably during or
after brushing your teeth. Pour approximately 20 ml of liquid (content
of two cups) into a glass, gargle for about 30 seconds and spit it out
afterwards. OROXID® sensitiv is suitable for a long-term use.

OTC Active Ingredient

hydrogen peroxide

Inactive Ingredient

deionized water,
Actipone® PX3, fl avors, stabilizer.

Storage

Store at temperature
of 5 °C to 25 °C

Keep reach of Children

Keep away from Children